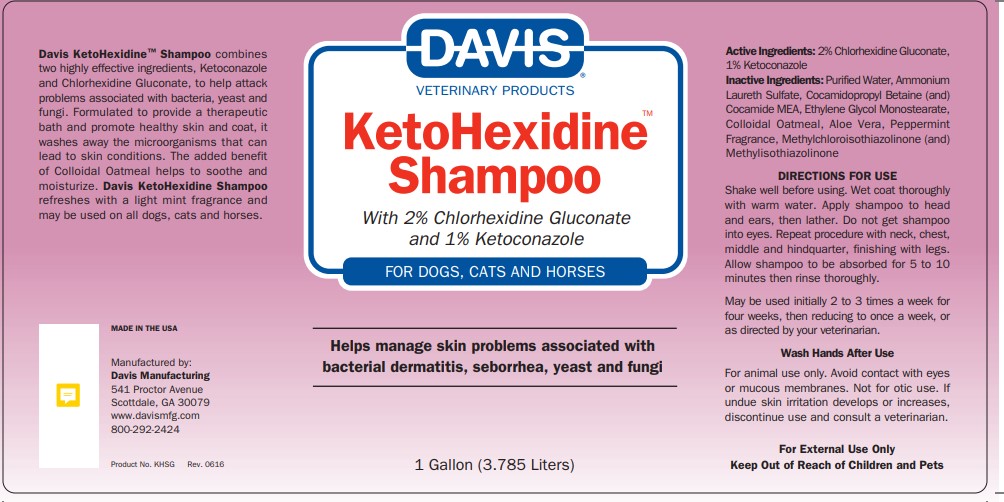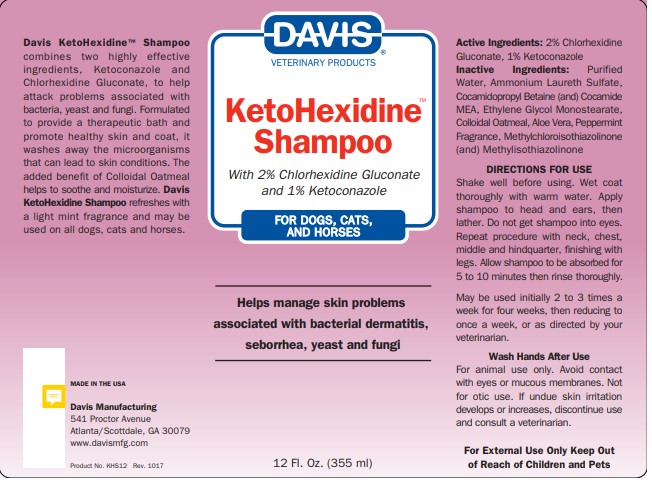 DRUG LABEL: Davis KetoHexidine
NDC: 62570-040 | Form: SHAMPOO
Manufacturer: Davis Manufacturing and Packaging Inc
Category: animal | Type: OTC ANIMAL DRUG LABEL
Date: 20230504

ACTIVE INGREDIENTS: CHLORHEXIDINE GLUCONATE 2 g/100 g; KETOCONAZOLE 1 g/100 g
INACTIVE INGREDIENTS: water; AMMONIUM LAURYL SULFATE; COCAMIDOPROPYL BETAINE; COCO MONOETHANOLAMIDE; GLYCOL STEARATE; OATMEAL; ALOE VERA LEAF; PEPPERMINT OIL; METHYLCHLOROISOTHIAZOLINONE/METHYLISOTHIAZOLINONE MIXTURE

Davis KetoHexidineTM Shampoo

DESCRIPTION

Davis KetoHexidineTM Shampoo combines two highly effective ingredients, Ketoconazole and Chlorhexidine Gluconate, to help attack problems associated with bacteria, yeast and fungi. Formulated to provide a therapeutic bath and promote healthy skin and coat, it washes away the microorganisms that can lead to skin conditions. The added benefit of Colloidal Oatmeal helps to soothe and moisturize. Davis KetoHexidine Shampoo refreshes with a light mint fragrance and may be used on all dogs, cats and horses.

MADE IN THE USA

Davis Manufacturing

541 Proctor Avenue

Scottdale, GA 30079 (Atlanta)

www.davismfg.com

Active Ingredients: 2% Chlorhexidine Gluconate, 1% Ketoconazole

INACTIVE INGREDIENT

Inactive Ingredients: Purified Water, Ammonium Laureth Sulfate, Cocamidopropyl Betaine (and) Cocamide MEA, Ethylene Glycol Monostearate, Colloidal Oatmeal, Aloe Vera, Peppermint Fragrance, Methylchloroisothiazolinone (and) Methylisothiazolinone

DIRECTIONS FOR USE

Shake well before using. Wet coat thoroughly with warm water. Apply shampoo to head and ears, then lather. Do not get shampoo into eyes. Repeat procedure with neck, chest, middle, and hindquarter, finishing with legs. Allow shampoo to be absorbed for 5 to 10 minutes then rinse thoroughly.

DOSAGE AND ADMINISTRATION

May be used initially 2 to 3 times a week for four weeks, then reducing to once a week, or as directed by your veterinarian.

WARNINGS AND PRECAUTIONS

Wash Hands After Use

For animal use only. Avoid contact with eyes or mucous membranes. Not for otic use. If undue skin irritation develops or increases, discontinue use and consult a veterinarian.

KEEP OUT OF REACH OF CHILDREN

For External Usse Only Keep Out of Reach of Children and Pets

PACKAGE LABEL

Davis Veterinary Products

KetoHexidineTMShampoo

with 2% Chlorhexidine Gluconate and 1%Ketoconazole

FOR DOGS, CATS, AND HORSES

Helps manage skin problems associated with bacterial dermititis, seborrhea, yeast and fungi

12 Fl. Oz. (355 ml)

PACKAGE LABEL

Davis Veterinary Products

KetoHexidineTM Shampoo

with 2% Chlorhexidine Gluconate and 1%Ketoconazole

FOR DOGS, CATS, AND HORSES

Helps manage skin problems associated with bacterial dermititis, seborrhea, yeast and fungi

1 Gallon (3.785 Liters)